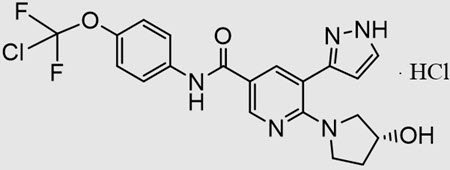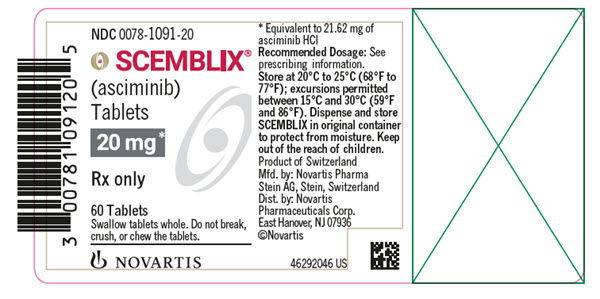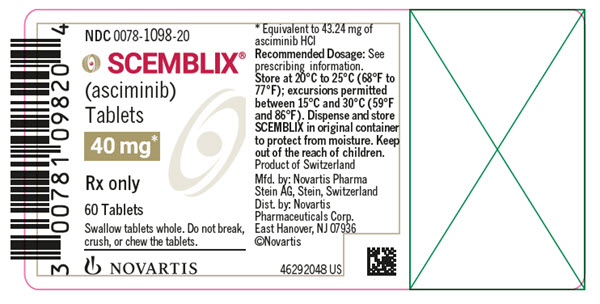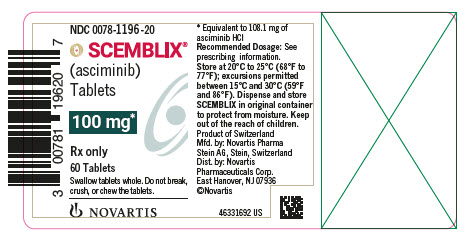 DRUG LABEL: SCEMBLIX
NDC: 0078-1091 | Form: TABLET, FILM COATED
Manufacturer: Novartis Pharmaceuticals Corporation
Category: prescription | Type: HUMAN PRESCRIPTION DRUG LABEL
Date: 20251125

ACTIVE INGREDIENTS: ASCIMINIB HYDROCHLORIDE 20 mg/1 1
INACTIVE INGREDIENTS: SILICON DIOXIDE; CROSCARMELLOSE SODIUM; HYDROXYPROPYL CELLULOSE, UNSPECIFIED; LACTOSE MONOHYDRATE; LECITHIN, SOYBEAN; MAGNESIUM STEARATE; CELLULOSE, MICROCRYSTALLINE; POLYVINYL ALCOHOL, UNSPECIFIED; TALC; TITANIUM DIOXIDE; XANTHAN GUM; FERRIC OXIDE YELLOW; FERRIC OXIDE RED

HIGHLIGHTS OF PRESCRIBING INFORMATION

These highlights do not include all the information needed to use SCEMBLIX safely and effectively. See full prescribing information for SCEMBLIX.
SCEMBLIX® (asciminib) tablets, for oral use
Initial U.S. Approval: 2021

1 INDICATIONS AND USAGE

SCEMBLIX is a kinase inhibitor indicated for the treatment of adult patients with:

- Newly diagnosed Philadelphia chromosome-positive chronic myeloid leukemia (Ph+ CML) in chronic phase (CP).
  This indication is approved under accelerated approval based on major molecular response rate. Continued approval for this indication may be contingent upon verification of clinical benefit in a confirmatory trial(s). (1)
- Previously treated Ph+ CML in CP. (1)
- Ph+ CML in CP with the T315I mutation. (1)

2 DOSAGE AND ADMINISTRATION

- Recommended Dosage in Ph+ CML in CP: 80 mg orally once daily or 40 mg orally twice daily. (2.1)
- Recommended Dosage in Ph+ CML in CP with the T315I Mutation: 200 mg orally twice daily. (2.2)
- Avoid food for at least 2 hours before and 1 hour after taking SCEMBLIX. (2.5)
- Swallow tablets whole. Do not break, crush, or chew the tablets. (2.5)

3 DOSAGE FORMS AND STRENGTHS

- Film-coated tablets: 20 mg, 40 mg, and 100 mg. (3)

4 CONTRAINDICATIONS

None. (4)

5 WARNINGS AND PRECAUTIONS

- Myelosuppression: Severe thrombocytopenia and neutropenia events may occur. Monitor complete blood counts regularly during therapy and manage by treatment interruption or dose reduction. (2.4, 5.1)
- Pancreatic Toxicity: Monitor serum lipase and amylase. Interrupt, then resume at reduced dose or discontinue SCEMBLIX based on severity. Evaluate for pancreatitis when lipase elevation is accompanied by abdominal symptoms. (2.4, 5.2)
- Hypertension: Monitor blood pressure and manage hypertension as clinically indicated. Interrupt, dose reduce, or stop SCEMBLIX if hypertension is not medically controlled. (2.4, 5.3)
- Hypersensitivity: May cause hypersensitivity reactions. Monitor patients for signs and symptoms and initiate appropriate treatment as clinically indicated. (5.4)
- Cardiovascular Toxicity: Cardiovascular toxicity may occur. Monitor patients with history of cardiovascular risk factors for cardiovascular signs and symptoms. Initiate appropriate treatment as clinically indicated. (5.5)
- Embryo-Fetal Toxicity: Can cause fetal harm. Advise females of reproductive potential of the potential risk to a fetus and to use effective contraception. (5.6, 8.1, 8.3)

6 ADVERSE REACTIONS

Most common adverse reactions (≥ 20%) are musculoskeletal pain, rash, fatigue, upper respiratory tract infection, headache, abdominal pain, arthralgia, and diarrhea. (6.1)

Most common select laboratory abnormalities (≥ 20%) are lymphocyte count decreased, leukocyte count decreased, platelet count decreased, neutrophil count decreased, calcium corrected decreased, lipase increased, cholesterol increased, uric acid increased, alanine aminotransferase (ALT) increased, alkaline phosphatase (ALP) increased, hemoglobin decreased, triglycerides increased, creatine kinase increased, amylase increased, and aspartate aminotransferase (AST) increased. (6.1)

To report SUSPECTED ADVERSE REACTIONS, contact Novartis Pharmaceuticals Corporation at 1-888-669-6682 or FDA at 1-800-FDA-1088 or www.fda.gov/medwatch.

7 DRUG INTERACTIONS

- Strong CYP3A4 Inhibitors: Closely monitor for adverse reactions during concomitant use of SCEMBLIX at 200 mg twice daily. (7.1)
- Itraconazole Oral Solution Containing Hydroxypropyl-β-cyclodextrin: Avoid concomitant use of SCEMBLIX at all recommended doses. (7.1)
- Certain Substrates of CYP3A4: Closely monitor for adverse reactions during concomitant use of SCEMBLIX at 80 mg total daily dose. Avoid use of SCEMBLIX at 200 mg twice daily. (7.2)
- Substrates of CYP2C9: Avoid concomitant use of SCEMBLIX at all recommended doses.
  - 80 mg total daily dose: If unavoidable, reduce the CYP2C9 substrate dosage as necessary. (7.2)
  - 200 mg twice daily: If unavoidable, consider alternative therapy with non-CYP2C9 substrate. (7.2)
- Certain P-gp Substrates: Closely monitor for adverse reactions during concomitant use of SCEMBLIX at all recommended doses. (7.2)
- Substrates of BCRP: Avoid concomitant use with rosuvastatin at all recommended doses. Closely monitor for adverse reactions of other BCRP substrates during concomitant use of SCEMBLIX at all recommended doses. (7.2)

8 USE IN SPECIFIC POPULATIONS

Lactation: Advise not to breastfeed. (8.2)

FULL PRESCRIBING INFORMATION

1 INDICATIONS AND USAGE

SCEMBLIX is indicated for the treatment of adult patients with:

- Newly diagnosed Philadelphia chromosome-positive chronic myeloid leukemia (Ph+ CML) in chronic phase (CP).
  This indication is approved under accelerated approval based on major molecular response rate [see Clinical Studies (14.1)]. Continued approval for this indication may be contingent upon verification of clinical benefit in a confirmatory trial(s).
- Previously treated Ph+ CML in CP.
- Ph+ CML in CP with the T315I mutation.

2 DOSAGE AND ADMINISTRATION

2.1 Recommended Dosage in Patients with Newly Diagnosed or Previously Treated Ph+ CML-CP

The recommended dose of SCEMBLIX is 80 mg taken orally once daily at approximately the same time each day or 40 mg orally twice daily at approximately 12-hour intervals. The recommended dose of SCEMBLIX is taken orally without food. Avoid food consumption for at least 2 hours before and 1 hour after taking SCEMBLIX [see Clinical Pharmacology (12.2)].

Continue treatment with SCEMBLIX as long as clinical benefit is observed or until unacceptable toxicity occurs.

2.2 Recommended Dosage in Patients with Ph+ CML-CP with the T315I Mutation

The recommended dose of SCEMBLIX is 200 mg taken orally twice daily at approximately 12-hour intervals. The recommended dose of SCEMBLIX is taken orally without food. Avoid food consumption for at least 2 hours before and 1 hour after taking SCEMBLIX [see Clinical Pharmacology (12.2)].

2.3 Missed Dose

Once Daily Dosage Regimen: If a SCEMBLIX dose is missed by more than approximately 12 hours, skip the dose and take the next dose as scheduled.

Twice Daily Dosage Regimens: If a SCEMBLIX dose is missed by more than approximately 6 hours, skip the dose and take the next dose as scheduled.

2.4 Dosage Modifications

Dosage Modifications for Patients with Newly Diagnosed or Previously Treated Ph+ CML-CP

For the management of adverse reactions, reduce the SCEMBLIX dose as described in Table 1.

Dosage Modifications for Patients with Ph+ CML-CP with the T315I Mutation

For the management of adverse reactions, reduce the SCEMBLIX dose as described in Table 1.

Table 1: Recommended Dosage Reductions for SCEMBLIX for Adverse Reactions
Dosage reduction | Dosage for Patients with newly diagnosed or previously treated Ph+ CML-CP | Dosage for patients with Ph+ CML-CP with the T315I mutation
First | - 40 mg once daily; OR; - 20 mg twice daily | 160 mg twice daily
Subsequent reduction | Permanently discontinue SCEMBLIX in patients unable to tolerate 40 mg once daily OR 20 mg twice daily. | Permanently discontinue SCEMBLIX in patients unable to tolerate 160 mg twice daily.

The recommended dosage modifications for the management of selected adverse reactions are shown in Table 2.

Table 2: SCEMBLIX Dosage Modification for the Management of Adverse Reactions
Adverse reaction | Dosage modification
Thrombocytopenia and/or neutropenia [see Warnings and Precautions (5.1)]
ANC less than 1 x 10^9/L and/or PLT less than 50 x 10^9/L | Withhold SCEMBLIX until resolved to ANC greater than or equal to 1 x 10^9/L and/or PLT greater than or equal to 50 x 10^9/L. If resolved:; - Within 2 weeks: resume SCEMBLIX at starting dose. - After more than 2 weeks: resume SCEMBLIX at reduced dose.; For recurrent severe thrombocytopenia and/or neutropenia, withhold SCEMBLIX until resolved to ANC greater than or equal to 1 x 10^9/L and PLT greater than or equal to 50 x 10^9/L, then resume at reduced dose.
Asymptomatic amylase and/or lipase elevation [see Warnings and Precautions (5.2)]
Elevation greater than 2 x ULN | Withhold SCEMBLIX until resolved to less than 1.5 x ULN. If resolved:; - Resume SCEMBLIX at reduced dose. If events reoccur at reduced dose, permanently discontinue SCEMBLIX.; If not resolved:; - Permanently discontinue SCEMBLIX. Perform diagnostic tests to exclude pancreatitis.
Non-hematologic adverse reactions [see Warnings and Precautions (5.3, 5.4, 5.5)]
Grade 3a or higher | Withhold SCEMBLIX until recovery to Grade 1 or less. If resolved:; - Resume SCEMBLIX at reduced dose.; If not resolved:; - Permanently discontinue SCEMBLIX.
Abbreviations: ANC, absolute neutrophil count; PLT, platelets; ULN, upper limit of normal.
aBased on Common Terminology Criteria for Adverse Events (CTCAE) version 4.03.

2.5 Administration

Advise patients to swallow SCEMBLIX tablets whole. Do not break, crush, or chew the tablets.

3 DOSAGE FORMS AND STRENGTHS

- 20 mg asciminib film-coated tablets: pale yellow, unscored, round, biconvex, with beveled edges, film-coated tablet debossed with “20” on one side and the “Novartis” logo on the other side.
- 40 mg asciminib film-coated tablets: violet white, unscored, round, biconvex, with beveled edges, film-coated tablet debossed with “40” on one side and the “Novartis” logo on the other side.
- 100 mg asciminib film-coated tablets: light red, unscored, round, biconvex, with beveled edges, film-coated tablet debossed with “100” on one side and the “Novartis” logo on the other side.

4 CONTRAINDICATIONS

None.

5 WARNINGS AND PRECAUTIONS

5.1 Myelosuppression

Thrombocytopenia, neutropenia, and anemia have occurred in patients receiving SCEMBLIX. Thrombocytopenia occurred in 156 of 556 (28%) patients receiving SCEMBLIX, with Grade 3 or 4 thrombocytopenia reported in 39 (7%) and 53 (10%) of patients, respectively. Among the patients with Grade 3 or 4 thrombocytopenia, median time to first occurrence of events was 6 weeks (range, 0.1 to 64 weeks). SCEMBLIX was permanently discontinued in 11 (2%) patients, while it was temporarily withheld in 70 (13%) patients due to thrombocytopenia.

Neutropenia occurred in 121 (22%) patients receiving SCEMBLIX, with Grade 3 and 4 neutropenia reported in 42 (8%) and 35 (6%) patients, respectively. Among the patients with Grade 3 or 4 neutropenia, median time to first occurrence of events was 7 weeks (range, 0.1 to 180 weeks). SCEMBLIX was permanently discontinued in 7 (1.3%) patients, while it was temporarily withheld in 52 (9%) patients due to neutropenia.

Anemia occurred in 72 (13%) patients receiving SCEMBLIX, with Grade 3 anemia occurring in 23 (4%) patients. Among the patients with Grade 3 or 4 anemia, median time to first occurrence of events was 24 weeks (range, 0.1 to 207 weeks). SCEMBLIX was temporarily withheld in 3 (0.5%) patients due to anemia [see Adverse Reactions (6.1)].

Perform complete blood counts every two weeks for the first 3 months of treatment and monthly thereafter or as clinically indicated. Monitor patients for signs and symptoms of myelosuppression.

Based on the severity of thrombocytopenia and/or neutropenia, reduce dose, temporarily withhold, or permanently discontinue SCEMBLIX [see Dosage and Administration (2.4)].

5.2 Pancreatic Toxicity

Pancreatitis occurred in 11 of 556 (2%) patients receiving SCEMBLIX, with Grade 3 pancreatitis occurring in 6 (1.1%) patients. SCEMBLIX was permanently discontinued in three (0.5%) patients, while it was temporarily withheld in 6 (1.1%) patients due to pancreatitis. Elevation of serum lipase and amylase occurred in 110 of 556 (20%) patients receiving SCEMBLIX, with Grade 3 and Grade 4 pancreatic enzyme elevations occurring in 41 (7%) and 11 (2%) patients, respectively. SCEMBLIX was permanently discontinued in 11 (2%) patients due to the elevation of serum lipase and amylase [see Adverse Reactions (6.1)].

Assess serum lipase and amylase levels monthly during treatment with SCEMBLIX, or as clinically indicated. Monitor patients for signs and symptoms of pancreatic toxicity. Perform more frequent monitoring in patients with a history of pancreatitis. If lipase and amylase elevation are accompanied by abdominal symptoms, temporarily withhold SCEMBLIX and consider appropriate diagnostic tests to exclude pancreatitis [see Dosage and Administration (2.4)].

Based on the severity of lipase and amylase elevation, reduce dose, temporarily withhold, or permanently discontinue SCEMBLIX [see Dosage and Administration (2.4)].

5.3 Hypertension

Hypertension occurred in 98 of 556 (18%) patients receiving SCEMBLIX, with Grade 3 or 4 hypertension reported in 53 (10%) and 1 (0.2%) patients, respectively. Among the patients with Grade 3 or 4 hypertension, median time to first occurrence was 45 weeks (range, 0.1 to 365 weeks). SCEMBLIX was temporarily withheld in 5 (0.9%) patients due to hypertension [see Adverse Reactions (6.1)].

Monitor and manage hypertension using standard antihypertensive therapy during treatment with SCEMBLIX as clinically indicated; for Grade 3 or higher hypertension, temporarily withhold, reduce dose, or permanently discontinue SCEMBLIX depending on persistence of hypertension [see Dosage and Administration (2.4)].

5.4 Hypersensitivity

Hypersensitivity occurred in 172 of 556 (31%) patients receiving SCEMBLIX, with Grade 3 or 4 hypersensitivity reported in 6 (1.1%) patients [see Adverse Reactions (6.1)]. Reactions included rash, edema, and bronchospasm. Monitor patients for signs and symptoms of hypersensitivity and initiate appropriate treatment as clinically indicated; for Grade 3 or higher hypersensitivity, temporarily withhold, reduce dose, or permanently discontinue SCEMBLIX depending on persistence of hypersensitivity [see Dosage and Administration (2.4)].

5.5 Cardiovascular Toxicity

Cardiovascular toxicity (including ischemic cardiac and CNS conditions, arterial thrombotic and embolic conditions) and cardiac failure occurred in 65 (12%) and in 13 (2.3%) of 556 patients receiving SCEMBLIX, respectively [see Adverse Reactions (6.1)]. Grade 3 cardiovascular toxicity was reported in 14 (2.5%) patients, while Grade 3 cardiac failure was observed in 5 (0.9%) patients. Grade 4 cardiovascular toxicity occurred in 4 (0.7%) patients, with fatalities occurring in 5 (0.9%) patients. Grade 4 cardiac failure was reported in 1 (0.2%) patient with fatality occurring in 1 (0.2%) patient. Permanent discontinuation of SCEMBLIX occurred in 4 (0.7%) patients due to cardiovascular toxicity and in 1 (0.2%) patient due to cardiac failure, respectively. In the majority of patients, cardiovascular toxicity occurred in patients with preexisting cardiovascular conditions or risk factors, and/or prior exposure to multiple TKIs.

Arrhythmia, including QTc prolongation, occurred in 35 of 556 (6%) patients receiving SCEMBLIX, with Grade 3 or 4 arrhythmia reported in 10 (1.8%) and 2 (0.4%) patients, respectively. QTc prolongation occurred in 5 of 556 (0.9%) patients receiving SCEMBLIX, with Grade 3 QTc prolongation reported in 2 (0.4%) patients [see Adverse Reactions (6.1)].

Monitor patients with history of cardiovascular risk factors for cardiovascular signs and symptoms. Initiate appropriate treatment as clinically indicated; for Grade 3 or higher cardiovascular toxicity, temporarily withhold, reduce dose, or permanently discontinue SCEMBLIX depending on persistence of cardiovascular toxicity [see Dosage and Administration (2.4)].

5.6 Embryo-Fetal Toxicity

Based on findings from animal studies and its mechanism of action, SCEMBLIX can cause fetal harm when administered to a pregnant woman. In animal reproduction studies, administration of asciminib to pregnant rats and rabbits during the period organogenesis caused adverse developmental outcomes, including embryo-fetal mortality and malformations at maternal exposures (AUC) equivalent to or less than those in patients at the recommended doses. Advise pregnant women and females of reproductive potential of the potential risk to a fetus if SCEMBLIX is used during pregnancy or if the patient becomes pregnant while taking SCEMBLIX. Verify the pregnancy status of females of reproductive potential prior to starting treatment with SCEMBLIX. Females of reproductive potential should use effective contraception during treatment with SCEMBLIX and for 1 week after the last dose [see Use in Specific Populations (8.1, 8.3)].

6 ADVERSE REACTIONS

The following clinically significant adverse reactions can occur with SCEMBLIX and are discussed in greater detail in other sections of the labeling:

- Myelosuppression [see Warnings and Precautions (5.1)]
- Pancreatic Toxicity [see Warnings and Precautions (5.2)]
- Hypertension [see Warnings and Precautions (5.3)]
- Hypersensitivity [see Warnings and Precautions (5.4)]
- Cardiovascular Toxicity [see Warnings and Precautions (5.5)]

6.1 Clinical Trials Experience

Because clinical trials are conducted under widely varying conditions, adverse reaction rates observed in the clinical trials of a drug cannot be directly compared to rates in the clinical trials of another drug and may not reflect the rates observed in practice.

The pooled safety population described in the WARNINGS AND PRECAUTIONS reflect exposure to SCEMBLIX at 10 mg to 200 mg orally twice daily (between 0.25 to 5 times the recommended dosage for the 80 mg daily dosage and between 0.05 times and up to the recommended dosage for the 200 mg twice daily dosage) in 556 patients enrolled in one of three clinical trials, including patients with Ph+ CML in CP receiving SCEMBLIX as monotherapy: study CABL001J12301 (ASC4FIRST), study CABL001A2301 (ASCEMBL) and study CABL001X2101 [see Clinical Studies (14)]. Among the 556 patients receiving SCEMBLIX, the median duration of exposure to SCEMBLIX was 123 weeks (range, 0.1 to 439 weeks), with 79% of patients exposed for at least 48 weeks and 71% of patients exposed for at least 96 weeks, respectively.

The most common (≥ 20%) adverse reactions in patients who received SCEMBLIX were musculoskeletal pain, rash, fatigue, upper respiratory tract infection, headache, abdominal pain, arthralgia, and diarrhea.

Adverse Reactions in Patients with Newly Diagnosed Ph+ CML-CP

The ASC4FIRST clinical trial randomized 405 patients with newly diagnosed Ph+ CML-CP to receive SCEMBLIX 80 mg once daily or investigator selected tyrosine kinase inhibitors (IS-TKIs). IS-TKIs included imatinib (400 mg once daily), nilotinib (300 mg twice daily), dasatinib (100 mg once daily), or bosutinib (400 mg once daily) [see Clinical Studies (14.1)]. The safety population (received at least 1 dose of SCEMBLIX) included 200 patients with newly diagnosed Ph+ CML-CP. Among patients who received SCEMBLIX, 84% were exposed for 96 weeks or longer [see Clinical Studies (14.1)].

Serious adverse reactions occurred in 15% of patients who received SCEMBLIX. Serious adverse reactions in ≥ 1% included pancreatitis (1%), musculoskeletal pain (1%), and peripheral neuropathy (1%).

Permanent discontinuation due to an adverse reaction occurred in 5% of patients receiving SCEMBLIX. Adverse reactions which resulted in permanent discontinuation of SCEMBLIX in ≥ 1% of patients included pancreatic enzymes increased (1.5%), cardiovascular toxicity (1%), and thrombocytopenia (1%).

Dosage interruptions of SCEMBLIX due to an adverse reaction occurred in 33% of patients. Adverse reactions which required dosage interruption in > 5% of patients included thrombocytopenia (13%) and neutropenia (10%).

Dose reductions of SCEMBLIX due to an adverse reaction occurred in 6% of patients. Adverse reactions which required dose reductions in > 1% of patients included thrombocytopenia (2.5%) and neutropenia (1.5%).

The most common (≥ 20%) adverse reactions in patients who received SCEMBLIX were musculoskeletal pain and rash.

The most common select laboratory abnormalities that worsened from baseline in ≥ 20% of patients who received SCEMBLIX were lymphocyte count decreased, leukocyte count decreased, platelet count decreased, neutrophil count decreased, calcium corrected decreased, lipase increased, cholesterol increased, uric acid increased, alanine aminotransferase (ALT) increased, alkaline phosphatase (ALP) increased, hemoglobin decreased, and triglycerides increased.

Table 3 summarizes the adverse reactions in ASC4FIRST.

Table 3: Adverse Reactions (≥ 10%) in Patients with Newly Diagnosed Ph+ CML in CP, Who Received SCEMBLIX in ASC4FIRST
 | SCEMBLIX N = 200 |  | IS-TKIs N = 201
Adverse Reaction | All Grades % | Grade 3 or 4 % | All Grades % | Grade 3 or 4 %
Musculoskeletal and connective tissue disorders
Musculoskeletal paina | 29 | 1.5 | 34 | 0.5
Arthralgia | 13 | 2 | 10 | 0.5
Skin and subcutaneous tissue disorders
Rashb | 20 | 0 | 27 | 2
General disorders and administration site conditions
Fatiguec | 19 | 1 | 22 | 1
Gastrointestinal disorders
Diarrhead | 18 | 0 | 28 | 1.5
Abdominal paine | 17 | 0.5 | 12 | 0.5
Constipation | 10 | 0 | 9 | 0.5
Infections and infestations
Upper respiratory tract infectionf | 18 | 0 | 20 | 0.5
Metabolism and nutrition disorders
Dyslipidemiag | 19 | 1 | 11 | 0.5
Nervous system disorders
Headacheh | 17 | 0.5 | 17 | 0
Vascular disorders
Hypertensioni | 11 | 6 | 6 | 4
Abbreviations: Ph+ CML in CP, Philadelphia chromosome-positive chronic myeloid leukemia (Ph+ CML) in chronic phase (CP); IS-TKIs, investigator selected tyrosine kinase inhibitors.
aMusculoskeletal pain includes: musculoskeletal pain, myalgia, pain in extremity, back pain, non-cardiac chest pain, bone pain, neck pain, musculoskeletal stiffness, musculoskeletal discomfort, musculoskeletal chest pain, arthritis, and spinal pain.
bRash includes: rash, rash maculo-papular, rash pustular, rash macular, dermatitis exfoliative, drug eruption, dermatitis acneiform, eczema, rash pruritic and rash vesicular.
cFatigue includes: fatigue and asthenia.
dDiarrhea includes: diarrhea, colitis and enteritis.
eAbdominal pain includes: abdominal pain, abdominal pain upper, abdominal discomfort, abdominal pain lower and gastrointestinal pain.
fUpper respiratory tract infection includes: upper respiratory tract infection, nasopharyngitis, pharyngitis, rhinitis and respiratory tract infection.
gDyslipidemia includes: dyslipidemia, hypertriglyceridemia, blood cholesterol increased, hypercholesterolemia, hyperlipidemia and blood triglycerides increased.
hHeadache contains: headache and migraine.
iHypertension contains: blood pressure increased, blood pressure systolic increased, diastolic hypertension, and hypertension.

Clinically relevant adverse reactions in < 10% of patients treated with SCEMBLIX in ASC4FIRST included: nausea, cough, pruritus, dry eye, pyrexia, vomiting, dizziness, edema, lower respiratory tract infection, decreased appetite, hypothyroidism, urticaria, arrhythmia, influenza, neuropathy peripheral, hemorrhage, urinary tract infection, pneumonia, dyspnea, pancreatitis, vision blurred, febrile neutropenia, and palpitations.

Table 4 summarizes the laboratory abnormalities in ASC4FIRST.

Table 4: Select Laboratory Abnormalities (≥ 20%) That Worsened From Baseline in Patients with Newly Diagnosed Ph+ CML in CP, Who Received SCEMBLIX in ASC4FIRST
 | SCEMBLIXa |  | IS-TKIsa
Laboratory Abnormality | All Grades % | Grade 3 or 4 % | All Grades % | Grade 3 or 4 %
Hematologic parameters
Lymphocyte count decreased | 72 | 3.5 | 84 | 11
Leukocyte count decreased | 55 | 5 | 68 | 13
Platelet count decreased | 48 | 13 | 56 | 11
Neutrophil count decreased | 47 | 12 | 63 | 21
Hemoglobin decreased | 25 | 3 | 51 | 5
Biochemical parameters
Calcium corrected decreased | 46 | 0.5 | 76 | 2
Lipase increased | 39 | 12 | 50 | 12
Cholesterol increased | 40 | 0 | 34 | 0
Uric acid increasedb | 37 | - | 22 | -
Alanine aminotransferase (ALT) increased | 33 | 2.5 | 45 | 6
Alkaline phosphatase (ALP) increased | 26 | 0.5 | 36 | 0
Triglycerides increased | 25 | 1 | 20 | 1.5
aThe denominator used to calculate the rate for SCEMBLIX and IS TKIs varied from 198 to 200 and 201, respectively, based on the number of patients with a baseline value and at least one post-treatment value.
bWorst post-baseline laboratory abnormalities based on normal ranges.
CTCAE version 5.0

Adverse Reactions in Patients with Ph+ CML-CP, Previously Treated with Two or More TKIs

The clinical trial randomized and treated 232 patients with Ph+ CML-CP, previously treated with two or more TKIs to receive SCEMBLIX 40 mg twice daily or bosutinib 500 mg once daily (ASCEMBL) [see Clinical Studies (14.2)]. The safety population (received at least 1 dose of SCEMBLIX) included 156 patients with Ph+ CML-CP, previously treated with two or more TKIs. Among patients who received SCEMBLIX, 83% were exposed for 24 weeks or longer and 56% were exposed for 96 weeks or longer.

Serious adverse reactions occurred in 18% of patients who received SCEMBLIX. Serious adverse reactions in ≥ 1% included cardiac failure congestive (1.9%), pyrexia (1.9%), urinary tract infection (1.9%), headache (1.3%), and thrombocytopenia (1.3%). Two patients (1.3%) had a fatal adverse reaction, one each for mesenteric artery thrombosis and ischemic stroke.

Permanent discontinuation of SCEMBLIX due to an adverse reaction occurred in 8% of patients. Adverse reactions which resulted in permanent discontinuation of SCEMBLIX in > 2% of patients included thrombocytopenia (3.2%) and neutropenia (2.6%).

Dosage interruptions of SCEMBLIX due to an adverse reaction occurred in 41% of patients. Adverse reactions which required dosage interruption in > 5% of patients included thrombocytopenia (19%) and neutropenia (18%).

Dose reductions of SCEMBLIX due to an adverse reaction occurred in 6% of patients. Adverse reactions which required dose reductions in > 1% of patients included thrombocytopenia (4.5%) and neutropenia (1.3%).

The most common (≥ 20%) adverse reactions in patients who received SCEMBLIX were upper respiratory tract infections, musculoskeletal pain, headache, and fatigue.

The most common select laboratory abnormalities that worsened from baseline in ≥ 20% of patients who received SCEMBLIX were platelet count decreased, triglycerides increased, neutrophil count decreased, hemoglobin decreased, creatine kinase increased, alanine aminotransferase (ALT) increased, aspartate aminotransferase (AST) increased, uric acid increased, and lymphocyte count decreased.

Table 5 summarizes the adverse reactions in ASCEMBL.

Table 5: Adverse Reactions (≥ 10%) in Patients with Ph+ CML in CP, Previously Treated with Two or More TKIs Who Received SCEMBLIX in ASCEMBL
 | SCEMBLIX N = 156 |  | Bosutinib N = 76
Adverse Reaction | All Grades % | Grade 3 or 4 % | All Grades % | Grade 3 or 4 %
Infections and infestations
Upper respiratory tract infectiona | 26 | 0.6 | 12 | 1.3
Musculoskeletal and connective tissue disorders
Musculoskeletal painb | 24 | 2.6 | 17 | 1.3
Arthralgia | 13 | 0.6 | 3.9 | 0
Nervous system disorders
Headachec | 21 | 1.9 | 16 | 0
General disorders and administration-site conditions
Fatigued | 20 | 0.6 | 11 | 1.3
Skin and subcutaneous tissue disorders
Rashe | 18 | 0.6 | 30 | 8
Vascular disorders
Hypertensionf | 14 | 7 | 5 | 3.9
Gastrointestinal disorders
Diarrheag | 13 | 0 | 72 | 11
Nausea | 12 | 0.6 | 46 | 0
Abdominal painh | 14 | 0 | 24 | 2.6
Abbreviations: Ph+ CML in CP, Philadelphia chromosome-positive chronic myeloid leukemia (Ph+ CML) in chronic phase (CP); TKIs, tyrosine kinase inhibitors.
aUpper respiratory tract infection includes: nasopharyngitis, upper respiratory tract infection, rhinitis, pharyngitis, respiratory tract infection, and pharyngotonsillitis.
bMusculoskeletal pain includes: pain in extremity, back pain, myalgia, non-cardiac chest pain, neck pain, bone pain, spinal pain, arthritis, musculoskeletal pain, and musculoskeletal chest pain.
cHeadache includes: headache and post-traumatic headache.
dFatigue includes: fatigue and asthenia.
eRash includes: rash, rash maculopapular, dermatitis acneiform, rash pustular, eczema, dermatitis, skin exfoliation, dermatitis exfoliative generalized, rash morbilliform, drug eruption, erythema multiforme, and rash erythematous.
fHypertension includes: hypertension and hypertensive crisis.
gDiarrhea includes: diarrhea and colitis.
hAbdominal pain includes: abdominal pain, abdominal pain upper, abdominal discomfort, abdominal pain lower, abdominal tenderness, and epigastric discomfort.

Clinically relevant adverse reactions in < 10% of patients treated with SCEMBLIX in ASCEMBL included: cough, dyspnea, pleural effusion, dizziness, neuropathy peripheral, edema, pyrexia, vomiting, constipation, dyslipidemia, decreased appetite, pruritus, urticaria, lower respiratory tract infection, influenza, urinary tract infection, pneumonia, hemorrhage, arrhythmia (including electrocardiogram QT prolonged), palpitations, cardiac failure congestive, vision blurred, dry eye, hypothyroidism, and febrile neutropenia.

Table 6 summarizes the laboratory abnormalities in ASCEMBL.

Table 6: Select Laboratory Abnormalities (≥ 10%) That Worsened From Baseline in Patients with Ph+ CML in CP, Previously Treated with Two or More TKIs Who Received SCEMBLIX in ASCEMBL
 | SCEMBLIXa |  | Bosutiniba
Laboratory Abnormality | All Grades % | Grade 3 or 4 % | All Grades % | Grade 3 or 4 %
Hematologic parameters
Platelet count decreased | 46 | 24 | 36 | 12
Neutrophil count decreased | 43 | 22 | 33 | 15
Hemoglobin decreased | 37 | 2 | 54 | 5
Lymphocyte count decreased | 20 | 3.3 | 34 | 2.6
Biochemical parameters
Triglycerides increased | 44 | 5 | 30 | 2.6
Creatine kinase increased | 30 | 2.6 | 24 | 5
Alanine aminotransferase (ALT) increased | 26 | 0.6 | 50 | 16
Aspartate aminotransferase (AST) increased | 21 | 1.9 | 46 | 7
Uric acid increased | 21 | 6 | 18 | 2.6
Phosphate decreased | 18 | 6 | 20 | 7
Corrected calcium decreased | 16 | 0.6 | 22 | 0
Lipase increased | 15 | 4.5 | 18 | 7
Creatinine increased | 15 | 0 | 26 | 0
Amylase increased | 13 | 1.3 | 13 | 0
Alkaline phosphatase (ALP) increased | 13 | 0 | 12 | 0
Bilirubin increased | 12 | 0 | 3.9 | 0
Cholesterol increased | 12 | 0 | 8 | 0
Potassium decreased | 11 | 0 | 9 | 0
aThe denominator used to calculate the rate for SCEMBLIX and bosutinib varied from 152 to 156 and 75 to 76, respectively, based on the number of patients with a baseline value and at least one post-treatment value.
CTCAE version 4.03.

Adverse Reactions in Patients with Ph+ CML-CP with the T315I Mutation

The single-arm clinical trial enrolled patients with Ph+ CML-CP with the T315I mutation [see Clinical Studies (14.3)]. The safety population (received at least 1 dose of SCEMBLIX) included 48 patients with Ph+ CML-CP with the T315I mutation who received 200 mg of SCEMBLIX twice daily. Among these patients, 83% were exposed for 24 weeks or longer, and 75% were exposed for 48 weeks or longer.

Serious adverse reactions occurred in 23% of patients who received SCEMBLIX. Serious adverse reactions in > 1% included abdominal pain (4.2%), vomiting (4.2%), pneumonia (4.2%), musculoskeletal pain (2.1%), headache (2.1%), hemorrhage (2.1%), constipation (2.1%), arrhythmia (2.1%), and pleural effusion (2.1%).

Permanent discontinuation of SCEMBLIX due to an adverse reaction occurred in 10% of patients. Adverse reactions which resulted in permanent discontinuation of SCEMBLIX in > 2% of patients included pancreatic enzymes increased (2.1%).

Dosage interruptions of SCEMBLIX due to an adverse reaction occurred in 31% of patients. Adverse reactions which required dosage interruption in > 5% of patients included pancreatic enzymes increased (17%) and thrombocytopenia (8%).

Dose reductions of SCEMBLIX due to an adverse reaction occurred in 23% of patients. Adverse reactions which required dose reductions in > 1% of patients included pancreatic enzymes increased (10%), abdominal pain (4.2%), anemia (2.1%), blood bilirubin increased (2.1%), dizziness (2.1%), fatigue (2.1%), hepatic enzymes increased (2.1%), musculoskeletal pain (2.1%), nausea (2.1%), neutropenia (2.1%), pruritus (2.1%), and thrombocytopenia (2.1%).

The most common (≥ 20%) adverse reactions in patients who received SCEMBLIX were musculoskeletal pain, fatigue, nausea, rash, and diarrhea.

The most common select laboratory abnormalities that worsened from baseline in ≥ 20% of patients who received SCEMBLIX were alanine aminotransferase (ALT) increased, lipase increased, triglycerides increased, hemoglobin decreased, neutrophil count decreased, lymphocyte count decreased, phosphate decreased, aspartate aminotransferase (AST) increased, amylase increased, platelet count decreased, and bilirubin increased.

Table 7 summarizes adverse reactions in study X2101.

Table 7: Adverse Reactions (≥ 10%) in Patients with Ph+ CML in CP with the T315I Mutation Who Received SCEMBLIX in X2101
 | SCEMBLIX 200 mg twice daily N = 48
Adverse Reaction | All Grades % | Grade 3 or 4 %
Musculoskeletal and connective tissue disorders
Musculoskeletal paina | 42 | 4.2
Arthralgia | 17 | 0
General disorders and administration-site conditions
Fatigueb | 31 | 2.1
Edema | 10 | 4.2
Gastrointestinal disorders
Nausea | 27 | 0
Diarrhea | 21 | 2.1
Vomiting | 19 | 6
Abdominal painc | 17 | 8
Skin and subcutaneous tissue disorders
Rashd | 27 | 0
Pruritus | 13 | 0
Nervous system disorders
Headachee | 19 | 2.1
Respiratory, thoracic, and mediastinal disorders
Coughf | 15 | 0
Vascular disorders
Hemorrhageg | 15 | 2.1
Hypertensionh | 13 | 8
Infections and infestations
Upper respiratory tract infectioni | 13 | 0
aMusculoskeletal pain includes: pain in extremity, back pain, myalgia, musculoskeletal pain, non-cardiac chest pain, bone pain, arthritis, and musculoskeletal chest pain.
bFatigue includes: fatigue and asthenia.
cAbdominal pain includes: abdominal pain and hepatic pain.
dRash includes: rash, rash maculopapular, dermatitis acneiform, eczema, rash papular, skin exfoliation, and dyshidrotic eczema.
eHeadache includes: headache and migraine.
fCough includes: cough and productive cough.
gHemorrhage includes: epistaxis, ear hemorrhage, mouth hemorrhage, post procedural hemorrhage, skin hemorrhage, and vaginal hemorrhage.
hHypertension includes: hypertension and hypertensive crisis.
iUpper respiratory tract infection includes: upper respiratory tract infection, nasopharyngitis, rhinitis, and pharyngitis.

Clinically relevant adverse reactions in < 10% of patients treated with SCEMBLIX in X2101 included: constipation, pancreatitis, pyrexia, dizziness, neuropathy peripheral, pneumonia, lower respiratory tract infection, dyspnea, pleural effusion, dry eye, vision blurred, arrhythmia, palpitations, cardiac failure congestive, decreased appetite, dyslipidemia, hypersensitivity, and urticaria.

Table 8 summarizes laboratory abnormalities in X2101.

Table 8: Select Laboratory Abnormalities (≥ 10%) That Worsened From Baseline in Patients with Ph+ CML in CP with the T315I Mutation in X2101
 | SCEMBLIXa 200 mg twice daily
Laboratory Abnormality | All Grades % | Grade 3-4 %
Hematologic parameters
Hemoglobin decreased | 44 | 4.2
Neutrophil count decreased | 44 | 15
Lymphocyte count decreased | 42 | 4.2
Platelet count decreased | 25 | 15
Biochemical parameters
Alanine aminotransferase (ALT) increased | 48 | 6
Potassium increased | 48 | 2.1
Triglycerides increased | 46 | 2.1
Lipase increased | 46 | 21
Phosphate decreased | 40 | 6
Uric acid increased | 40 | 4.2
Aspartate aminotransferase (AST) increased | 35 | 2.1
Calcium corrected decreased | 33 | 0
Creatinine increased | 31 | 0
Amylase increased | 29 | 10
Bilirubin increased | 23 | 0
Cholesterol increased | 15 | 0
Alkaline phosphatase (ALP) increased | 13 | 0
aThe denominator used to calculate the rate was 48 based on the number of patients with a baseline value and at least one post-treatment value.
CTCAE version 4.03.

7 DRUG INTERACTIONS

7.1 Effect of Other Drugs on SCEMBLIX

Strong CYP3A4 Inhibitors

Asciminib is a CYP3A4 substrate. Concomitant use of SCEMBLIX with a strong CYP3A4 inhibitor increases both the asciminib Cmax and AUC, which may increase the risk of adverse reactions [see Clinical Pharmacology (12.3)]. Closely monitor for adverse reactions in patients treated with SCEMBLIX at 200 mg twice daily with concomitant use of strong CYP3A4 inhibitors.

Itraconazole Oral Solution Containing Hydroxypropyl-β-cyclodextrin

Concomitant use of SCEMBLIX with itraconazole oral solution containing hydroxypropyl-β-cyclodextrin decreases asciminib Cmax and AUC, which may reduce SCEMBLIX efficacy [see Clinical Pharmacology (12.3)]. Avoid coadministration of SCEMBLIX at all recommended doses with itraconazole oral solution containing hydroxypropyl-β-cyclodextrin.

Strong CYP3A4 Inducers

Concomitant use of SCEMBLIX with strong CYP3A4 inducers decreases both the asciminib Cmax and AUC [see Clinical Pharmacology (12.3)].

7.2 Effect of SCEMBLIX on Other Drugs

Certain CYP3A4 Substrates

Asciminib is a CYP3A4 inhibitor. Concomitant use of SCEMBLIX increases the Cmax and AUC of CYP3A4 substrates, which may increase the risk of adverse reactions of these substrates [see Clinical Pharmacology (12.3)].

Closely monitor for adverse reactions in patients treated with SCEMBLIX at 80 mg total daily dose with concomitant use of certain CYP3A4 substrates, where minimal concentration changes may lead to serious adverse reactions. Avoid coadministration of SCEMBLIX at 200 mg twice daily with certain CYP3A4 substrates, where minimal concentration changes may lead to serious adverse reactions.

CYP2C9 Substrates

Asciminib is a CYP2C9 inhibitor. Concomitant use of SCEMBLIX increases the Cmax and AUC of CYP2C9 substrates, which may increase the risk of adverse reactions of these substrates [see Clinical Pharmacology (12.3)].

Avoid coadministration of SCEMBLIX at 80 mg total daily dose with certain CYP2C9 substrates, where minimal concentration changes may lead to serious adverse reactions. If coadministration is unavoidable, reduce the CYP2C9 substrate dosage as recommended in its prescribing information.

Avoid coadministration of SCEMBLIX at 200 mg twice daily with sensitive CYP2C9 substrates and certain CYP2C9 substrates, where minimal concentration changes may lead to serious adverse reactions. If coadministration is unavoidable, consider alternative therapy with a non-CYP2C9 substrate.

Certain P-gp Substrates

Asciminib is a P-gp inhibitor. Concomitant use of SCEMBLIX increases the plasma concentrations of P-gp substrates, which may increase the risk of adverse reactions of these substrates [see Clinical Pharmacology (12.3)].

Closely monitor for adverse reactions in patients treated with SCEMBLIX at all recommended doses with concomitant use of P-gp substrates, where minimal concentration changes may lead to serious toxicities.

Substrates of BCRP

Asciminib is a BCRP inhibitor. Concomitant use of SCEMBLIX may increase the plasma concentration of BCRP substrates [see Clinical Pharmacology (12.3)], which may increase the risk of adverse reactions associated with these substrates.

Avoid coadministration of SCEMBLIX at all recommended doses with rosuvastatin. Closely monitor for adverse reactions in patients treated with SCEMBLIX at all recommended doses with concomitant use of other BCRP substrates. Reduce the dosage of the other BCRP substrates as recommended in their Prescribing Information when used concomitantly with SCEMBLIX at all recommended doses.

8 USE IN SPECIFIC POPULATIONS

8.1 Pregnancy

Risk Summary

Based on findings from animal studies and the mechanism of action, SCEMBLIX can cause embryo-fetal harm when administered to a pregnant woman [see Clinical Pharmacology (12.1)]. There are no available data on SCEMBLIX use in pregnant women to evaluate a drug-associated risk.

Animal reproduction studies in pregnant rats and rabbits demonstrated that oral administration of asciminib during organogenesis induced structural abnormalities, embryo-fetal mortality, and alterations to growth (see Data).

Advise pregnant women and females of reproductive potential of the potential risk to a fetus.

In the U.S. general population, the estimated background risk of major birth defects and miscarriage in clinically recognized pregnancies is 2% to 4% and 15% to 20%, respectively.

Data

Animal Data

In embryo-fetal development studies, pregnant animals received oral doses of asciminib at 25, 150, and 600 mg/kg/day in rats and at 15, 50, and 300 mg/kg/day in rabbits during the period of organogenesis.

In rats, maternal toxicity at the asciminib dose of 600 mg/kg/day resulted in the early termination of the dose group; a complete embryo-fetal examination was not conducted for this group. Adverse embryo-fetal findings were observed at 25 and 150 mg/kg; these doses did not cause maternal toxicities. Increases in fetal weights at 25 and 150 mg/kg/day were observed, which may be related to increased ossification (i.e., increased rate of development). Malformations were evident at 150 mg/kg and included cleft palate, anasarca (edema), and cardiac abnormalities. Additional fetal findings included urinary tract and skeletal variations, observed primarily at 150 mg/kg/day. At the dose of 25 mg/kg/day, the area under the curve (AUC) exposures were equivalent to or below those achieved in patients at the 40 mg twice daily or 80 mg once daily doses, respectively. At the dose of 25 mg/kg/day, the AUC exposures were below those achieved in patients at the 200 mg twice daily dose.

In rabbits, maternal toxicities at the asciminib dose of 300 mg/kg/day resulted in the early termination of the dose group; a complete embryo-fetal examination was not conducted for this group. Adverse embryo-fetal findings were observed at 50 mg/kg; this dose did not cause maternal toxicities. Findings at the 50 mg/kg dose included increases in early resorptions and post-implantation loss, decreases in the number of live fetuses, and cardiac malformations. At the dose of 50 mg/kg/day, the AUC exposures were 4-fold those achieved in patients at the 40 mg twice daily or 80 mg once daily doses. At the dose of 50 mg/kg/day, the AUC exposures were below those achieved in patients at the 200 mg twice daily dose.

8.2 Lactation

Risk Summary

There are no data on the presence of asciminib or its metabolites in human milk, the effects on the breastfed child, or milk production.

Because of the potential for serious adverse reactions in the breastfed child, advise women not to breastfeed during treatment with SCEMBLIX and for 1 week after the last dose.

8.3 Females and Males of Reproductive Potential

Based on findings from animal studies, SCEMBLIX can cause embryo-fetal harm when administered to a pregnant woman [see Use in Specific Populations (8.1)].

Pregnancy Testing

Verify the pregnancy status of females of reproductive potential prior to starting treatment with SCEMBLIX.

Contraception

Females

Females of reproductive potential should use effective contraception during treatment with SCEMBLIX and for 1 week after the last dose.

Infertility

Based on findings in animals, SCEMBLIX may impair fertility in females of reproductive potential [see Nonclinical Toxicology (13.1)]. The reversibility of the effect on fertility is unknown.

8.4 Pediatric Use

The safety and efficacy of SCEMBLIX in pediatric patients have not been established.

8.5 Geriatric Use

Among the 556 patients receiving SCEMBLIX in the ASC4FIRST, ASCEMBL and X2101 studies, 130 (23%) were 65 years of age and older and 31 (6%) were 75 years of age and older.

Overall, no differences in safety or efficacy of SCEMBLIX were observed between patients 65 years of age and older compared to younger patients.

8.6 Renal Impairment

No dose adjustment is required for patients with mild to severe renal impairment (estimated glomerular filtration rate [eGFR] 15 to 89 mL/min/1.73 m^2) and not requiring dialysis receiving SCEMBLIX [see Clinical Pharmacology (12.3)].

8.7 Hepatic Impairment

No dose adjustment is required for patients with mild [total bilirubin ≤ upper limit of normal (ULN) and aspartate aminotransferase (AST) > ULN or total bilirubin > 1 to 1.5 times ULN and any AST] to severe hepatic impairment (total bilirubin > 3 times ULN and any AST) receiving SCEMBLIX [see Clinical Pharmacology (12.3)].

11 DESCRIPTION

SCEMBLIX (asciminib) is a kinase inhibitor. The chemical name of the drug substance is N-[4-(Chlorodifluoromethoxy)phenyl]-6-[(3R)-3-hydroxypyrrolidin-1-yl]-5-(1H-pyrazol-3-yl)pyridine-3-carboxamide-hydrogen chloride (1/1). Asciminib hydrochloride is a white to slightly yellow powder. The molecular formula of asciminib hydrochloride is C20H18ClF2N5O3.HCl, and the relative molecular mass is 486.30 g/mol for the hydrochloride salt and 449.84 g/mol for the free base. The chemical structure of asciminib hydrochloride is shown below:

SCEMBLIX film-coated tablets are supplied for oral use with three strengths that contain 20 mg, 40 mg and 100 mg of asciminib (equivalent to 21.62 mg, 43.24 mg and 108.10 mg, respectively, of asciminib hydrochloride). The tablets contain colloidal silicon dioxide, croscarmellose sodium, ferric oxide, hydroxypropyl cellulose, lactose monohydrate, lecithin, magnesium stearate, microcrystalline cellulose, polyvinyl alcohol, talc, titanium dioxide, and xanthan gum. The 20 mg tablets contain ferric oxide, yellow and ferric oxide, red. The 40 mg and 100 mg tablets contain ferrosoferric oxide and ferric oxide, red.

12 CLINICAL PHARMACOLOGY

12.1 Mechanism of Action

Asciminib is an ABL/BCR-ABL1 tyrosine kinase inhibitor. Asciminib inhibits the ABL1 kinase activity of the BCR::ABL1 fusion protein, by binding to the ABL myristoyl pocket. In studies conducted in vitro or in animal models of CML, asciminib showed activity against wild-type BCR::ABL1 and several mutant forms of the kinase, including the T315I mutation.

12.2 Pharmacodynamics

Exposure-Response Relationships

Over asciminib dosages of 10 mg to 200 mg twice daily (0.25 to 5 times the recommended 80 mg daily dosage), a lower exposure was associated with a smaller decrease in BCR::ABL1 level and a lower MMR rate at Week 24.

Over asciminib dosages of 10 mg to 280 mg twice daily (0.25 to 7 times the recommended 80 mg daily dosage), a higher exposure was associated with slightly higher incidence of some adverse reactions (e.g., Grade ≥ 3 lipase increase, Grade ≥ 3 hemoglobin decrease, Grade ≥ 2 ALT increase, Grade ≥ 2 AST increase, Grade ≥ 2 bilirubin increase, and any grade lipase increase).

Cardiac Electrophysiology

Asciminib does not cause a large mean increase in QTc interval (i.e., > 20 msec) at the maximum recommended clinical dosage (200 mg twice daily). Based on available clinical data, small mean QTc increase (< 10 msec) cannot be excluded.

12.3 Pharmacokinetics

Asciminib steady-state exposure (AUC and Cmax) increase slightly more than dose proportional across the dose range of 10 to 200 mg (0.25 to 5 times the recommended 80 mg daily dosage) administered once or twice daily.

Pharmacokinetic parameters are presented as geometric mean (CV%) unless otherwise stated. The steady state Cmax and AUCtau of asciminib at recommended dosages are listed in Table 9.

Table 9: Steady Statea Asciminib Exposure at Recommended Dosages
Asciminib dosage | Cmax (ng/mL) | AUCtaub (ng*h/mL) | Accumulation ratio
80 mg once daily | 1781 (23%) | 15112 (28%) | 1.30
40 mg twice daily | 793 (49%) | 5262 (48%) | 1.65
200 mg twice daily | 5642 (40%) | 37547 (41%) | 1.92
aSteady state is achieved within 3 days.
bAUCtau represents AUC0-12h for twice daily dosing and AUC0-24h for once daily dosing.

Absorption

The median (range) Tmax of asciminib is 2.5 hours (2 to 3 hours).

Effect of Food

The AUC and Cmax of asciminib decreased by 62% and 68%, respectively, with a high-fat meal (1000 calories, 50% fat) and by 30% and 35%, respectively, with a low-fat meal (400 calories, 25% fat) compared to the fasted state following administration of SCEMBLIX.

Distribution

The apparent volume of distribution of asciminib at steady state is 151 L (135%). Asciminib is the main circulating component in plasma (93% of the administered dose).

Asciminib is 97% bound to human plasma proteins in vitro.

Elimination

The total apparent clearance of asciminib is 6.7 L/hour (48%) at 40 mg twice daily and 80 mg once daily, and 4.1 L/hour (38%) at 200 mg twice daily. The terminal elimination half-life of asciminib is 5.5 hours (38%) at 40 mg twice daily and 80 mg once daily, and 9.0 hours (33%) at 200 mg twice daily.

Metabolism

Asciminib is metabolized by CYP3A4-mediated oxidation, UGT2B7- and UGT2B17-mediated glucuronidation.

Excretion

Eighty percent (57% as unchanged) and 11% (2.5% as unchanged) of the asciminib dose were recovered in the feces and in the urine of healthy subjects, respectively, following oral administration of a single 80 mg dose of radio-labeled asciminib.

Asciminib is eliminated by biliary secretion via breast cancer-resistant protein (BCRP).

Specific Populations

No clinically significant differences in the pharmacokinetics of asciminib were observed based on sex, age (20 to 88 years), race (Asian 20%, White 70%, Black/African American 4%), or body weight (42-184 kg), mild to moderate renal impairment (eGFR 30 to 89 mL/min/1.73 m^2), or mild (total bilirubin ≤ ULN and AST > ULN or total bilirubin > 1 to 1.5 times ULN and any AST) to moderate (total bilirubin > 1.5 to 3 times ULN and any AST) hepatic impairment.

Patients with Renal Impairment

Asciminib AUCinf and Cmax are increased by 57% and 6%, respectively, in subjects with eGFR between 13 to < 30 mL/min/1.73 m^2 and not requiring dialysis compared to subjects with normal renal function (eGFR ≥ 90 mL/min/1.73 m^2) following oral administration of a single 40 mg dose of SCEMBLIX. The exposure changes in patients with severe renal impairment are not considered clinically meaningful.

Patients with Hepatic Impairment

Asciminib AUCinf and Cmax are increased by 33% and 4%, respectively, in subjects with severe hepatic impairment (total bilirubin > 3 times ULN and any AST), compared to subjects with normal hepatic function (total bilirubin ≤ ULN and AST ≤ ULN) following oral administration of a single 40 mg dose of SCEMBLIX. The exposure changes are not considered clinically meaningful.

Drug Interaction Studies

Clinical Studies and Model-Informed Approaches

Drugs That Affect Asciminib Plasma Concentration

Strong CYP3A Inhibitors: The asciminib AUCinf and Cmax increased by 36% and 19%, respectively, following coadministration of a single SCEMBLIX dose of 40 mg with a strong CYP3A4 inhibitor (clarithromycin). No clinically significant differences in the pharmacokinetics of asciminib were observed when coadministered with itraconazole, which is also a strong CYP3A4 inhibitor.

Strong CYP3A Inducers: The asciminib AUCinf decreased by 34% and Cmax decreased by 22% following coadministration of a single SCEMBLIX dose of 200 mg with a strong CYP3A4 inducer (phenytoin) 100 mg three times daily. The asciminib AUCinf decreased by 15% while Cmax increased by 9%, following coadministration of a single SCEMBLIX dose of 40 mg with a strong CYP3A4 inducer (rifampicin).

Itraconazole Oral Solution: Coadministration of multiple doses of itraconazole oral solution containing hydroxypropyl-β-cyclodextrin with a single SCEMBLIX dose of 40 mg decreased asciminib AUCinf and Cmax by 40% and 50%, respectively. Concomitant use of oral products containing hydroxypropyl-β-cyclodextrin with SCEMBLIX other than itraconazole oral solution has not been fully characterized.

Imatinib: The asciminib AUCinf and Cmax increase by 108% and 59%, respectively following coadministration of a single SCEMBLIX dose of 40 mg with imatinib (an inhibitor of BCRP, CYP3A4, UGT2B17, and UGT1A3/4). The exposure changes are not considered clinically meaningful. Concomitant use of imatinib with SCEMBLIX at 200 mg twice daily has not been fully characterized.

Other Drugs: No clinically significant differences in the pharmacokinetics of asciminib were observed when coadministered with rabeprazole (acid-reducing agent) and quinidine (P-gp inhibitor).

Drugs That are Affected by Asciminib

CYP3A4 Substrates: The midazolam AUCinf and Cmax increased by 28% and 11%, respectively, following coadministration of a CYP3A4 substrate (midazolam) with SCEMBLIX 40 mg twice daily. The midazolam AUCinf and Cmax increased by 24% and 17%, respectively, following coadministration with SCEMBLIX at 80 mg once daily and 88% and 58%, respectively, at 200 mg twice daily.

CYP2C9 Substrates: The S-warfarin AUCinf and Cmax increased by 41% and 8%, respectively, following coadministration of CYP2C9 substrate (warfarin) with SCEMBLIX at 40 mg twice daily. The S-warfarin AUCinf and Cmax increased by 52% and 4%, respectively, following coadministration with SCEMBLIX at 80 mg once daily and 314% and 7%, respectively, at 200 mg twice daily.

CYP2C8 Substrates: The repaglinide (substrate of CYP2C8, CYP3A4, and OATP1B) AUCinf and Cmax increased by 8% and 14%, respectively, following coadministration of repaglinide with SCEMBLIX 40 mg twice daily. The repaglinide AUCinf and Cmax increased by 12% and 8%, respectively, following coadministration with SCEMBLIX at 80 mg once daily and 42% and 25%, respectively, at 200 mg twice daily. The rosiglitazone (substrate of CYP2C8 and CYP2C9) AUCinf and Cmax increased by 20% and 3%, respectively, following coadministration of rosiglitazone with SCEMBLIX 40 mg twice daily. The rosiglitazone AUCinf and Cmax increased by 24% and 2%, respectively, following coadministration with SCEMBLIX at 80 mg once daily and 66% and 8%, respectively, at 200 mg twice daily.

P-gp Substrates: Coadministration of SCEMBLIX with a drug that is a substrate of P-gp may result in a clinically relevant increase in the plasma concentrations of P-gp substrates, where minimal concentration changes may lead to serious toxicities.

OATP1B Substrates: The atorvastatin (substrate of OATP1B, CYP3A4, and P-gp) AUCinf and Cmax increased by 14% and 24%, respectively, following coadministration of atorvastatin with SCEMBLIX 80 mg once daily.

In Vitro Studies

CYP450 and UGT Enzymes

Asciminib may reversibly inhibit UGT1A1 at plasma concentrations reached at a total daily dose of 80 mg and 200 mg twice daily. In addition, asciminib may reversibly inhibit CYP2C19 at concentrations reached at 200 mg twice daily dose.

Transporter Systems

Asciminib is a substrate of BCRP and P-gp. Asciminib inhibits BCRP, P-gp, OATP1B1, OATP1B3, and OCT1. Asciminib may increase the exposure of BCRP substrates in a dose dependent manner.

13 NONCLINICAL TOXICOLOGY

13.1 Carcinogenesis, Mutagenesis, Impairment of Fertility

In a 2-year carcinogenicity study, rats were administered oral doses of asciminib at 20, 66, and 200 mg/kg/day in males and 10, 30, and 66 mg/kg/day in females. Asciminib induced a statistically significant increase in the incidence of benign Sertoli cell tumors in the ovaries of high-dose females. The exposures to asciminib (AUC) in female rats at 66 mg/kg/day were approximately 8-fold or 6-fold higher than the exposure (AUC) achieved in patients at the dose of 40 mg twice daily or 80 mg once daily, respectively, and equivalent to those achieved in patients at the dose of 200 mg twice daily. The clinical relevance of these findings is currently unknown.

Asciminib was not genotoxic in an in vitro bacterial mutagenicity (Ames) assay, an in vitro micronucleus assay in human peripheral blood lymphocytes (HPBL), or an in vivo rat peripheral blood reticulocyte micronucleus assay.

In a combined male and female fertility and early embryonic development study in rats, animals were administered asciminib doses of 10, 50, or 200 mg/kg/day orally. Male animals were dosed once daily for at least 28 days prior to mating, during the 2-week mating period, and until terminal necropsy (Days 63-67). Female animals were dosed once daily for the 2-week premating period, during the 2-week mating period, and through gestation day (GD) 6. Decreased sperm count and motility were observed at 200 mg/kg/day. While there were no effects on fertility indices or conception rates, a decreased mean number of live embryos was observed at 200 mg/kg/day and was attributed to a lower number of implantations and an increased number of early resorptions. Increased early resorptions were also observed in the embryo-fetal development study in rabbits [see Use in Specific Populations (8.1)].

At the dose of 200 mg/kg, the AUC exposures were approximately 19-fold, 13-fold, or 2-fold higher than those achieved in patients at the 40 mg twice daily, 80 mg once daily, or 200 mg twice daily doses, respectively.

14 CLINICAL STUDIES

14.1 Newly Diagnosed Ph+ CML-CP

The efficacy of SCEMBLIX in the treatment of patients with newly diagnosed Ph+ CML in chronic phase (Ph+ CML-CP) was evaluated in the multi-center, randomized, active-controlled, and open-label study ASC4FIRST (NCT04971226).

In this study, a total of 405 patients were randomized in a 1:1 ratio to receive either SCEMBLIX or investigator selected tyrosine kinase inhibitors (IS-TKIs). Prior to randomization, the investigator selected the TKI (imatinib, nilotinib, dasatinib, or bosutinib) to be used in the event of randomization to the comparator arm, based on patient characteristics and comorbidities. Patients were stratified according to EUTOS long-term survival (ELTS) risk group (low, intermediate, high), and pre-randomization selection of TKI (imatinib or other TKIs stratum composed of nilotinib, dasatinib, and bosutinib). Patients received either SCEMBLIX or IS-TKIs, and continued treatment until unacceptable toxicity or treatment failure occurred.

Patients were 37% female and 63% male with median age 51 years (range, 18 to 86 years). Of the 405 patients, 24% were 65 years or older, while 6% were 75 years or older. Patients were White (54%), Asian (44%), Black or African American (1%), and 1% unknown.

Of the 405 patients, 200 received SCEMBLIX, while 201 received IS-TKIs. Of the 201 patients receiving IS-TKIs, 99 received imatinib, 49 received nilotinib, 42 received dasatinib, and 11 received bosutinib. Four patients did not receive any treatment.

The median duration of treatment was 27 months (range, 0.2 to 36 months) for patients receiving SCEMBLIX, and 25 months (range, 0.3 to 35 months) for patients receiving IS-TKIs. With a minimum of 96 weeks of follow-up, 82% of patients on SCEMBLIX, and 60% of patients on IS-TKIs were still receiving treatment.

The main efficacy outcome was major molecular response rate (MMR) at 48 weeks. Efficacy was established based on SCEMBLIX compared to IS-TKIs and SCEMBLIX compared to IS-TKIs within the imatinib stratum. The key secondary objective evaluated MMR at 96 weeks for SCEMBLIX compared both to IS-TKIs and to IS-TKIs within the imatinib stratum. Secondary objectives evaluated MMR at 48 and 96 weeks for SCEMBLIX compared to IS-TKIs within the other TKIs stratum. The main efficacy outcomes from ASC4FIRST are summarized in Table 10.

Table 10: Efficacy Results in Patients with Newly Diagnosed Ph+ CML-CP (ASC4FIRST)
Response | SCEMBLIX 80 mg once daily All patients (N = 201) | IS-TKIsa All patients (N = 204) | Difference (95% CI)b | p-value
MMR at 48 weeks MMR (%) (95% CI) | 68 (61, 74) | 49 (42, 56) | 19 (10, 28) | < 0.001c
MMR at 96 weeks MMR (%) (95% CI) | 74 (68, 80) | 52 (45, 59) | 22 (14, 31) | < 0.001c
Response | SCEMBLIX 80 mg once daily Imatinib stratum (N = 101) | IS-TKIsa Imatinib stratum (N = 102) | Difference (95% CI)b | p-value
MMR at 48 weeks MMR (%) (95% CI) | 69 (59, 78) | 40 (31, 50) | 30 (17, 42) | < 0.001d
MMR at 96 weeks MMR (%) (95% CI) | 76 (67, 84) | 47 (37, 57) | 30 (18, 42) | < 0.001d
Abbreviations: MMR, major molecular response (BCR::ABL1IS ≤ 0.1%); IS-TKIs, investigator selected tyrosine kinase inhibitors.
aIS-TKIs include imatinib (400 mg once daily) and other TKIs of nilotinib (300 mg twice daily), dasatinib (100 mg once daily) or bosutinib (400 mg once daily).
bEstimated using a common risk difference stratified by PRS-TKI and baseline ELTS risk groups.
cAdjusted p-value using a Cochran-Mantel-Haenszel 1-sided test stratified by PRS-TKI and baseline ELTS risk groups.
dAdjusted p-value using a Cochran-Mantel-Haenszel 1-sided test stratified by baseline ELTS risk groups.

MMR rates at 96 weeks in patients receiving SCEMBLIX and IS-TKIs within the other TKIs stratum were 72% (95% CI: 62%, 81%) and 57% (95% CI: 47%, 67%), respectively.

Median time to MMR in patients receiving SCEMBLIX, IS-TKIs, and IS-TKIs within the imatinib stratum were: 24 weeks (95% CI: 24 to 25 weeks), 36 weeks (95% CI: 36 to 49 weeks), and 49 weeks (95% CI: 36 to 60 weeks), respectively.

14.2 Ph+ CML-CP, Previously Treated with Two or More TKIs

The efficacy of SCEMBLIX in the treatment of patients with Ph+ CML-CP, previously treated with two or more TKIs was evaluated in the multi-center, randomized, active-controlled, and open-label study ASCEMBL (NCT03106779).

In this study, a total of 233 patients were randomized in a 2:1 ratio and stratified according to major cytogenetic response (MCyR) status to receive either SCEMBLIX 40 mg twice daily (N = 157) or bosutinib 500 mg once daily (N = 76). Patients continued treatment until unacceptable toxicity or treatment failure occurred.

Patients were 52% female and 48% male with a median age of 52 years (range, 19 to 83 years). Of the 233 patients, 19% were 65 years or older, while 2.6% were 75 years or older. Patients were White (75%), Asian (14%), and Black or African American (4.3%). Of the 233 patients, 81% and 18% had Eastern Cooperative Oncology Group (ECOG) performance status 0 or 1, respectively. Patients who had previously received 2, 3, 4, or 5 or more prior lines of TKIs were 48%, 31%, 15%, and 6%, respectively. The median duration of treatment was 103 weeks (range, 0.1 to 201 weeks) for patients receiving SCEMBLIX and 31 weeks (range, 1 to 188 weeks) for patients receiving bosutinib.

The main efficacy outcomes from ASCEMBL are summarized in Table 11.

Table 11: Efficacy Results in Patients with Ph+ CML-CP, Previously Treated with Two or More TKIs (ASCEMBL)
 | SCEMBLIX 40 mg twice daily | Bosutinib 500 mg once daily | Difference (95% CI) | p-value
MMR rate, % (95% CI) at 24 weeks | N = 157 25 (19, 33) | N = 76 13 (6.5, 23) | 12a (2.2, 22) | 0.029b
MMR rate, % (95% CI) at 96 weeks | N = 157 38 (30, 46) | N = 76 16 (8, 26) | 22a (11, 33) | 0.001b
CCyR rate, % (95% CI) at 24 weeks | N = 103c 41 (31, 51) | N = 62c 24 (14, 37) | 17 (3.6, 31)
CCyR rate, % (95% CI) at 96 weeks | N = 103c 40 (30, 50) | N = 62c 16 (8, 28) | 24a (10, 37)
Abbreviations: MMR, major molecular response (BCR::ABL1IS ≤ 0.1%); CCyR, complete cytogenetic response (0% of Philadelphia-positive metaphases in bone marrow aspirate with at least 20 examined).
aEstimated using a common risk difference stratified by baseline major cytogenetic response status.
bEstimated using a Cochran-Mantel-Haenszel two-sided test stratified by baseline major cytogenetic response status.
cCCyR analysis based on patients who were not in CCyR at baseline.

With a median duration of follow-up of 28 months (range, 1 day to 45 months), the median duration of response for patients treated with SCEMBLIX had not yet been reached.

14.3 Ph+ CML-CP with the T315I Mutation

The efficacy of SCEMBLIX in the treatment of patients with Ph+ CML-CP with the T315I mutation was evaluated in a multi-center open-label study CABL001X2101 (NCT02081378). Testing for T315I mutation utilized a qualitative p210 BCR::ABL1 mutation test on peripheral blood using Sanger Sequencing.

Efficacy was based on 45 patients with Ph+ CML-CP with the T315I mutation who received SCEMBLIX at a dose of 200 mg twice daily. Patients continued treatment until unacceptable toxicity or treatment failure occurred.

Of the 45 patients, 80% were male and 20% female; 31% were 65 years or older, while 9% were 75 years or older with a median age of 54 years (range, 26 to 86 years). The patients were White (47%), Asian (27%), and Black or African American (2.2%), and 24% were unreported or unknown. Seventy-three percent and 27% of patients had ECOG performance status 0 and 1, respectively. Patients who had previously received 1, 2, 3, 4, and 5 or more TKIs were 18%, 31%, 36%, 13%, and 2.2%, respectively. MMR was achieved by 24 weeks in 42% (19/45, 95% CI: 28% to 58%) of the 45 patients treated with SCEMBLIX. MMR was achieved by 96 weeks in 49% (22/45, 95% CI: 34% to 64%) of the 45 patients treated with SCEMBLIX. The median duration of treatment was 108 weeks (range, 2 to 215 weeks).

16 HOW SUPPLIED/STORAGE AND HANDLING

SCEMBLIX tablets are available as:

Table 12: SCEMBLIX Package Configurations and NDC Numbers
Package configuration | Tablet strength | NDC number
Bottle of 60 tablets | 20 mg | NDC 0078-1091-20
Bottle of 60 tablets | 40 mg | NDC 0078-1098-20
Bottle of 60 tablets | 100 mg | NDC 0078-1196-20

- SCEMBLIX (asciminib) 20 mg film-coated tablets are supplied as pale yellow, unscored, round, biconvex, with beveled edges, film-coated tablets containing 20 mg of asciminib. Each tablet is debossed with “20” on one side and the “Novartis” logo on the other side.
- SCEMBLIX (asciminib) 40 mg film-coated tablets are supplied as violet white, unscored, round, biconvex, with beveled edges, film-coated tablets containing 40 mg of asciminib. Each tablet is debossed with “40” on one side and the “Novartis” logo on the other side.
- SCEMBLIX (asciminib) 100 mg film-coated tablets are supplied as light red, unscored, round, biconvex, with beveled edges, film-coated tablets containing 100 mg of asciminib. Each tablet is debossed with “100” on one side and the “Novartis” logo on the other side.

Store at 20°C to 25°C (68°F to 77°F); excursions permitted between 15°C and 30°C (59°F and 86°F) [see USP Controlled Room Temperature]. Dispense and store in the original container in order to protect from moisture.

17 PATIENT COUNSELING INFORMATION

Advise the patient to read the FDA-approved patient labeling (Patient Information).

Myelosuppression

Inform patients of the possibility of developing low blood cell counts. Advise patients to immediately report fever, any suggestion of infection, or signs or symptoms suggestive of bleeding or easy bruising [see Warnings and Precautions (5.1)].

Pancreatic Toxicity

Inform patients of the possibility of developing pancreatitis that may be accompanied by nausea, vomiting, severe abdominal pain, or abdominal discomfort, and to promptly report these symptoms [see Warnings and Precautions (5.2)].

Hypertension

Inform patients of the possibility of developing hypertension. Advise patients to contact their healthcare provider for elevated blood pressure or if symptoms of hypertension occur, including confusion, headache, dizziness, chest pain, or shortness of breath [see Warnings and Precautions (5.3)].

Hypersensitivity

Advise the patient to discontinue SCEMBLIX and seek immediate medical attention if any signs or symptoms of a hypersensitivity reaction, such as rash, edema, or bronchospasm occur [see Warnings and Precautions (5.4)].

Cardiovascular Toxicity

Inform patients of the possibility of the occurrence of cardiovascular toxicity, especially those with a history of cardiovascular risk factors. Advise patients to immediately contact their healthcare provider or get medical help if they develop cardiovascular signs and symptoms [see Warnings and Precautions (5.5)].

Embryo-Fetal Toxicity

Advise females to inform their healthcare provider if they are pregnant or become pregnant. Inform female patients of the potential risk to a fetus [see Use in Specific Populations (8.1)].

Advise females of reproductive potential to use effective contraception during treatment and for 1 week after receiving the last dose of SCEMBLIX [see Warnings and Precautions (5.6), Use in Specific Populations (8.1, 8.3)].

Lactation

Advise women not to breastfeed during treatment with SCEMBLIX and for 1 week after the last dose [see Use in Specific Populations (8.2)].

Infertility

Advise females of reproductive potential of the potential for impaired fertility from SCEMBLIX [see Use in Specific Populations (8.3), Nonclinical Toxicology (13.1)].

Drug Interactions

Advise patients that SCEMBLIX and certain other medicines, including over-the-counter medications or herbal supplements, can interact with each other and may alter the effects of SCEMBLIX [see Drug Interactions (7)].

Instructions for Taking SCEMBLIX

Advise patients to take SCEMBLIX exactly as prescribed and not to change their dose or schedule or to stop taking SCEMBLIX unless they are told to do so by their healthcare provider.

Advise patients to take SCEMBLIX orally without food. Advise patients to avoid food for at least 2 hours before and 1 hour after taking SCEMBLIX. SCEMBLIX tablets should be swallowed whole. Patients should not break, crush, or chew the tablets [see Dosage and Administration (2.5)].

Advise patients that if they take SCEMBLIX once daily and miss a dose by more than 12 hours to skip the missed dose. Advise patients that if they take SCEMBLIX twice daily and miss a dose by more than 6 hours to skip the missed dose. Advise patients to take the next dose as scheduled [see Dosage and Administration (2.3)].

Distributed by:
Novartis Pharmaceuticals Corporation
One Health Plaza
East Hanover, New Jersey 07936

© Novartis

T2025-68

PATIENT INFORMATION
SCEMBLIX® (sem blix)
(asciminib) tablets

What is SCEMBLIX?
SCEMBLIX is a prescription medicine used to treat adults with:

- newly diagnosed or previously treated Philadelphia chromosome-positive chronic myeloid leukemia (Ph+ CML) in chronic phase (CP).
- Ph+ CML in CP with the T315I mutation.

It is not known if SCEMBLIX is safe and effective in children.

Before taking SCEMBLIX, tell your healthcare provider about all of your medical conditions, including if you:

- have a history of inflammation of your pancreas (pancreatitis)
- have a history of heart problems or blood clots in your arteries and veins (types of blood vessels)
- are pregnant or plan to become pregnant. SCEMBLIX can harm your unborn baby.
  Females who are able to become pregnant:
  - Your healthcare provider will do a pregnancy test before you start treatment with SCEMBLIX.
  - You should use effective birth control (contraception) during treatment and for 1 week after your last dose of SCEMBLIX. Talk to your healthcare provider about birth control methods that may be right for you.
  - Tell your healthcare provider right away if you become pregnant or think you may be pregnant during treatment with SCEMBLIX.
- are breastfeeding or plan to breastfeed. It is not known if SCEMBLIX passes into your breast milk. Do not breastfeed during treatment and for 1 week after your last dose of SCEMBLIX.

Tell your healthcare provider about all the medicines you take, including prescription and over-the-counter medicines, vitamins, and herbal supplements.
Taking SCEMBLIX with certain other medicines may affect each other causing side effects and may affect the way that SCEMBLIX works.

How should I take SCEMBLIX?

- Take SCEMBLIX exactly as your healthcare provider tells you to take it.
- Do not change your dose or schedule or stop taking SCEMBLIX unless your healthcare provider tells you to.
- Take SCEMBLIX without food. You should avoid eating for at least 2 hours before and 1 hour after taking SCEMBLIX.
- Swallow SCEMBLIX tablets whole. Do not break, crush, or chew SCEMBLIX tablets.
- If you take SCEMBLIX 1 time a day and miss a dose by more than 12 hours, skip the missed dose and take your next dose at your regular time.
- If you take SCEMBLIX 2 times a day and miss a dose by more than 6 hours, skip the missed dose and take your next dose at your regular time.

What are the possible side effects of SCEMBLIX?
SCEMBLIX may cause serious side effects, including:

- Low blood cell counts. SCEMBLIX may cause low platelet counts (thrombocytopenia), low white blood cell counts (neutropenia), and low red blood cell counts (anemia). Your healthcare provider will do blood tests to check your blood cell counts every 2 weeks for the first 3 months of treatment and then monthly or as needed during treatment with SCEMBLIX. Tell your healthcare provider right away if you have unexpected bleeding or easy bruising, blood in your urine or stools, fever, or any signs of an infection.
- Pancreas problems. SCEMBLIX may increase enzymes in your blood called amylase and lipase, which may be a sign of inflammation of the pancreas (pancreatitis). Your healthcare provider may do blood tests monthly or as needed during treatment with SCEMBLIX to check for problems with your pancreas. Tell your healthcare provider right away if you have severe stomach-area (abdominal) pain or discomfort, nausea, or vomiting.
- High blood pressure. Your healthcare provider may check your blood pressure and treat any high blood pressure during treatment with SCEMBLIX as needed. Tell your healthcare provider if you develop high blood pressure or symptoms of high blood pressure, including confusion, headaches, dizziness, chest pain, or shortness of breath.
- Allergic reaction. Stop taking SCEMBLIX and get medical help right away if you get any signs or symptoms of an allergic reaction, including:

○ trouble breathing or swallowing
○ swelling of the face, lips, or tongue
○ skin rash or flushing of your skin

○ feeling dizzy or faint
○ fever
○ fast heartbeat

- Heart and blood vessel (cardiovascular) problems. SCEMBLIX may cause heart and blood vessel problems, including heart attack, stroke, blood clots or blockage of your arteries, heart failure, and abnormal heartbeat, which can be serious and may sometimes lead to death. In the majority of cases, these heart and blood vessel problems happened in people with risk factors or a history of these problems, and previously treated with other tyrosine kinase inhibitor (TKI) medicines. Your healthcare provider may monitor you for heart and blood vessel problems and treat you as needed during treatment with SCEMBLIX. Tell your healthcare provider or get medical help right away if you get:

○ shortness of breath
○ chest pain or pressure
○ feeling like your heart is beating too fast or you feel abnormal heartbeats
○ swelling in your ankles or feet
○ dizziness

○ weight gain
○ numbness or weakness on one side of your body
○ decreased vision or loss of vision
○ trouble talking
○ pain in your arms, legs, back, neck or jaw
○ headache
○ severe stomach-area (abdominal) pain

The most common side effects of SCEMBLIX include:

• muscle, bone, or joint pain
• rash
• tiredness
• nose, throat, or sinus (upper respiratory tract) infections
• headache
• stomach-area (abdominal) pain
• diarrhea

• decreased white blood cell counts, platelet counts, and red blood cell counts
• decreased blood calcium corrected levels
• increased blood pancreas enzyme (lipase and amylase) levels
• increased blood fat (cholesterol and triglycerides) levels
• increased blood uric acid levels
• increased blood liver enzyme levels
• increased blood alkaline phosphatase levels
• increased blood creatine kinase levels

Your healthcare provider may change your dose or temporarily or permanently stop treatment with SCEMBLIX if you have certain side effects.
SCEMBLIX may cause fertility problems in females. This may affect your ability to have a child. Talk to your healthcare provider if this is a concern for you.
These are not all of the possible side effects of SCEMBLIX.
Call your doctor for medical advice about side effects. You may report side effects to FDA at 1-800-FDA-1088.

How should I store SCEMBLIX?

- Store SCEMBLIX at room temperature between 68°F to 77°F (20°C to 25°C).
- Store SCEMBLIX in the original container to protect it from moisture.

Keep SCEMBLIX and all medicines out of the reach of children.

General information about the safe and effective use of SCEMBLIX.
Medicines are sometimes prescribed for purposes other than those listed in a Patient Information leaflet. Do not use SCEMBLIX for a condition for which it was not prescribed. Do not give SCEMBLIX to other people, even if they have the same symptoms you have. It may harm them. You can ask your pharmacist or healthcare provider for more information about SCEMBLIX that is written for health professionals.

What are the ingredients in SCEMBLIX?
Active ingredient: asciminib
Inactive ingredients: colloidal silicon dioxide, croscarmellose sodium, ferric oxide, hydroxypropyl cellulose, lactose monohydrate, lecithin, magnesium stearate, microcrystalline cellulose, polyvinyl alcohol, talc, titanium dioxide, and xanthan gum. The 20 mg tablets contain ferric oxide, yellow and ferric oxide, red. The 40 mg and 100 mg tablets contain ferrosoferric oxide and ferric oxide, red.
Distributed by: Novartis Pharmaceuticals Corporation, One Health Plaza, East Hanover, New Jersey 07936
For more information, go to www.SCEMBLIX.com or call 1-888-669-6682.

This Patient Information has been approved by the U.S. Food and Drug Administration.

Revised: 10/2024

© Novartis

T2024-79

PRINCIPAL DISPLAY PANEL

NDC 0078-1091-20

SCEMBLIX®

(asciminib)
Tablets

20 mg*

Rx only

60 Tablets

Swallow tablets whole. Do not break,
crush, or chew the tablets.

NOVARTIS

PRINCIPAL DISPLAY PANEL

NDC 0078-1098-20

SCEMBLIX®

(asciminib)
Tablets

40 mg*

Rx only

60 Tablets

Swallow tablets whole. Do not break,
crush, or chew the tablets.

NOVARTIS

PRINCIPAL DISPLAY PANEL

NDC 0078-1196-20

SCEMBLIX®

(asciminib)
Tablets

100 mg*

Rx only

60 Tablets

Swallow tablets whole. Do not break,
crush, or chew the tablets.

NOVARTIS